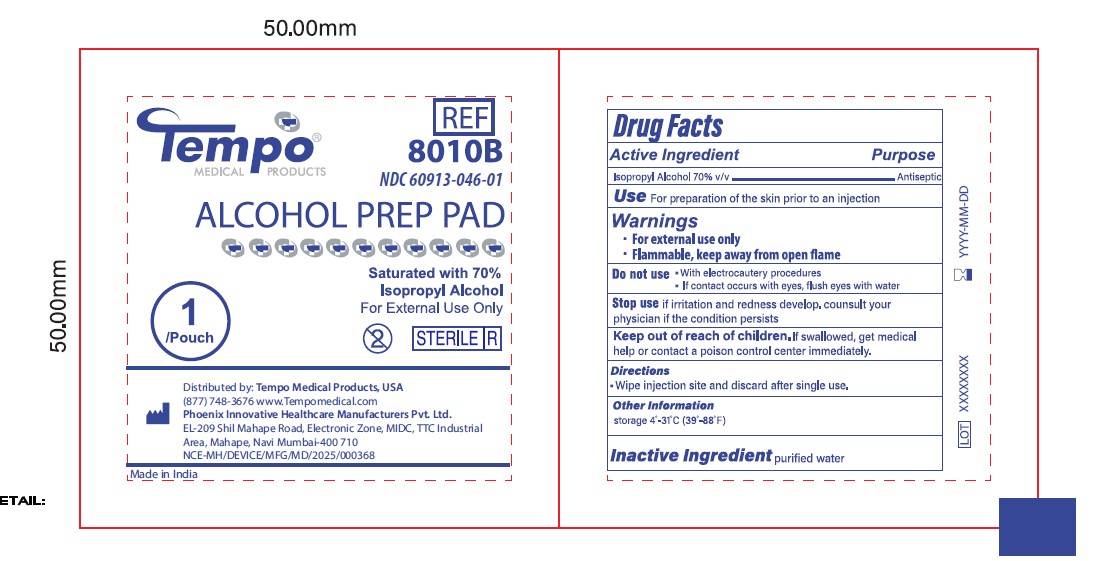 DRUG LABEL: Alcohol Prep Pads
NDC: 60913-046 | Form: SWAB
Manufacturer: Phoenix Healthcare Solutions LLC
Category: otc | Type: HUMAN OTC DRUG LABEL
Date: 20251023

ACTIVE INGREDIENTS: ISOPROPYL ALCOHOL 70 mL/100 mL
INACTIVE INGREDIENTS: WATER

Tempo APP 460ct Medium

Active Ingredients

Isopropyl alcohol 70% v/v

Purpose

Antiseptic

Use

For preparation of the skin prior to injection; to decrease germs in minor cuts and scrapes.

Warnings

For external use only. Flammable; keep away from fire and flame.

OTC - KEEP OUT OF REACH OF CHILDREN SECTION

If swallowed, get medical help or contact a Poison Control Center immediately.

Caution

Do not apply to irritated skin.

Do not use

in the eyes, or on mucous membranes. In case of deep or puncture wounds, consult a doctor.

Directions

Wipe injection site vigorously.

Other information

Store at room temperature

Inactive Ingredient Section

Water

Principal Display Panel